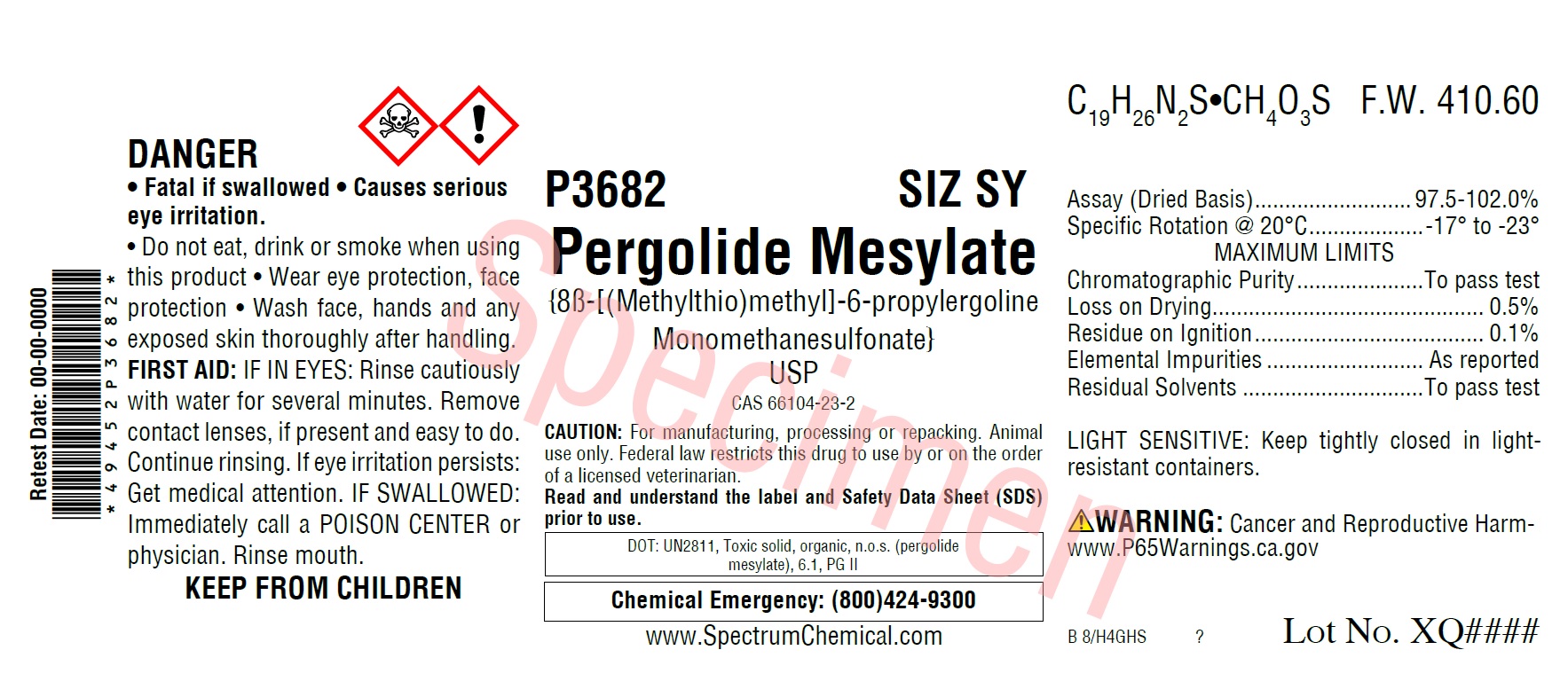 DRUG LABEL: Pergolide Mesylate
NDC: 49452-5115 | Form: POWDER
Manufacturer: Spectrum Laboratory Products, Inc.
Category: other | Type: BULK INGREDIENT
Date: 20210126

ACTIVE INGREDIENTS: PERGOLIDE MESYLATE 1 g/1 g

Pergolide Mesylate